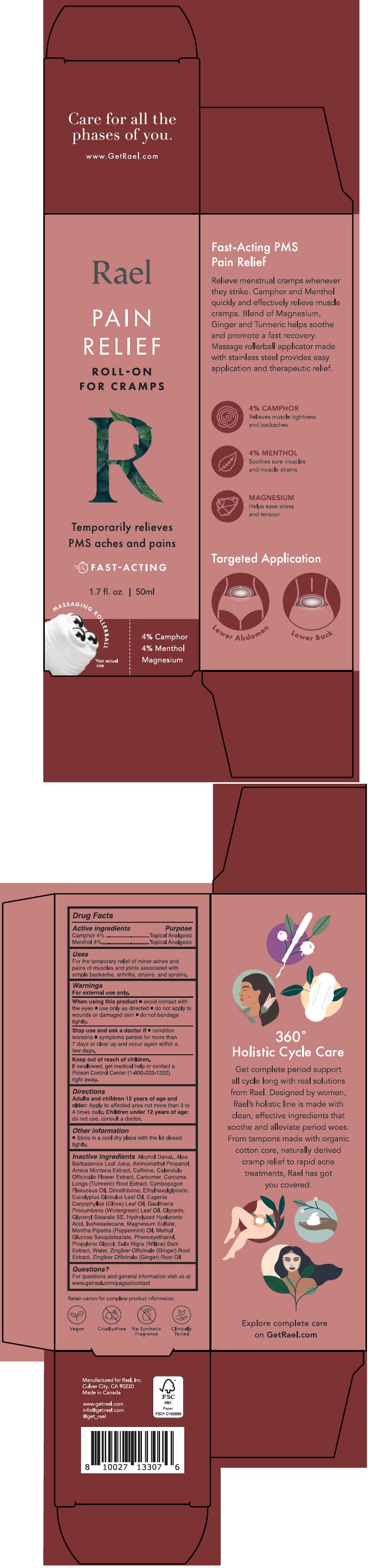 DRUG LABEL: Rael PAIN RELIEF ROLL-ON
NDC: 72863-076 | Form: LIQUID
Manufacturer: Rael, Inc.
Category: otc | Type: HUMAN OTC DRUG LABEL
Date: 20241028

ACTIVE INGREDIENTS: CAMPHOR (SYNTHETIC) 40 mg/1 mL; MENTHOL, UNSPECIFIED FORM 40 mg/1 mL
INACTIVE INGREDIENTS: ALCOHOL; ALOE VERA LEAF; AMINOMETHYLPROPANOL; ARNICA MONTANA WHOLE; Caffeine; CALENDULA OFFICINALIS FLOWER; CARBOMER HOMOPOLYMER, UNSPECIFIED TYPE; TURMERIC; EAST INDIAN LEMONGRASS OIL; Dimethicone; Ethylhexylglycerin; EUCALYPTUS OIL; CLOVE LEAF OIL; METHYL SALICYLATE; Glycerin; Glyceryl Stearate SE; HYALURONIC ACID (NON-ANIMAL STABILIZED); Isohexadecane; MAGNESIUM SULFATE, UNSPECIFIED FORM; PEPPERMINT OIL; Methyl Glucose Sesquistearate; Phenoxyethanol; Propylene Glycol; SALIX NIGRA BARK; Water; GINGER; GINGER OIL

Rael PAIN RELIEF ROLL-ON
Topical Analgesic

Drug Facts

ACTIVE INGREDIENT

Active ingredients | Purpose
Camphor 4% | Topical analgesic
Menthol 4% | Topical analgesic

Uses

For the temporary relief of minor aches and pains of muscles and joints associated with simple backache, arthritis, strains, and sprains.

Warnings

For external use only

When using this product

- avoid contact with the eyes
- use only as directed
- do not apply to wounds or damaged skin
- do not bandage tightly.

Stop use and ask a doctor if

- condition worsens
- symptoms persist for more than 7 days or clear up and occur again within a few days.

Keep out of reach of children.

If swallowed, get medical help or contact a Poison Control Center (1-800-222-1222) right away.

Directions

Adults and children 12 years of age and older: Apply to affected area not more than 3 to 4 times daily. Children under 12 years of age: do not use, consult a doctor.

Other information

- store in a cool dry place with the lid closed tightly.

Inactive ingredients

Alcohol Denat, Aloe Barbadensis Leaf Juice, Aminomethyl Propanol, Arnica Montana Extract, Caffeine, Calendula Officinalis Flower Extract, Carbomer, Curcuma Longa (Turmeric) Root Extract, Cymbopogon Flexuosus Oil, Dimethicone, Ethylhexylglycerin, Eucalyptus Globulus Leaf Oil, Eugenia Caryophyllus (Clove) Leaf Oil, Gaultheria Procumbens (Wintergreen) Leaf Oil, Glycerin, Glyceryl Stearate Se, Hydrolyzed Hyaluronic Acid, Isohexadecane, Magnesium Sulfate, Mentha Piperita (Peppermint) Oil, Methyl Glucose Sesquistearate, Phenoxyethanol, Propylene Glycol, Salix Nigra (Willow) Bark Extract, Water, Zingiber Officinale (Ginger) Root Extract, Zingiber Officinale (Ginger) Root Oil

Questions?

For questions and general information visit us at www.getrael.com/pages/contact

PRINCIPAL DISPLAY PANEL - 50 mL Bottle Carton

Rael

PAIN
RELIEF

ROLL-ON
FOR CRAMPS

R

Temporarily relieves
PMS aches and pains

FAST-ACTING

1.7 fl. oz. | 50ml

MASSAGING ROLLERBALL

*Not actual
size

4% Camphor
4% Menthol
Magnesium